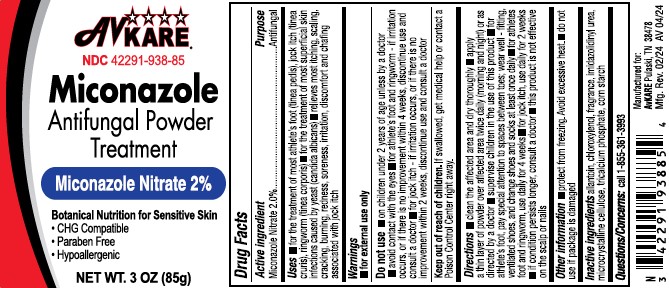 DRUG LABEL: Miconazole Nitrate
NDC: 42291-938 | Form: POWDER
Manufacturer: AvKARE
Category: otc | Type: HUMAN OTC DRUG LABEL
Date: 20260119

ACTIVE INGREDIENTS: MICONAZOLE NITRATE 2 g/100 g
INACTIVE INGREDIENTS: ALLANTOIN; CHLOROXYLENOL; IMIDUREA; MICROCRYSTALLINE CELLULOSE; TRICALCIUM PHOSPHATE; STARCH, CORN

Miconazole Nitrate 2%

Drug Facts

Active ingredient

Miconazole Nitrate 2.0%

Purpose

Antifungal

Uses

- for the treatment of most athlete's foot (tinea pedis), jock itch (tinea cruris), ringworm (tinea corporis)
- for the treatment of most superficial skin infections caused by yeast (candida albicans)
- relieves most itching, scaling, cracking, burning, redness, soreness, irritation, discomfort and chafing associated with jock itch

Warnings

- for external use only

Do not use

- on children under 2 years of age unless by a doctor
- avoid contact with the eyes
- for athlete's foot and ringworm - if irritation occurs, or if there is no improvement within 4 weeks, discontinue use and consult a doctor
- for jock itch - if irritation occurs, or if there is no improvement within 2 weeks, dicontinue use and consult a doctor

Keep out of reach of children.If swallowed, get medical help or contact a Poison Control Center right away.

Directions

- clean the affected area and dry thoroughly
- apply a thin layer of powder over affected area twice daily (morning and night) or as directed by a doctor
- supervise children in the use of this product
- for athlete's foot, pay special attention to spaces between toes; wear well - fitting, ventilated shoes, and change shoes and socks at least once daily
- for athletes foot and ringworm, use daily for 4 weeks
- for jock itch, use daily for 2 weeks
- if condition persists longer, consult a doctor
- this product is not effective on the scalp or nails

Other information

- protect from freezing. Avoid excessive heat.
- do not use if package is damaged

Inactive ingredients

allantoin, chloroxylenol, fragrance, imidazolidinyl urea, microcrystalline cellulose, tricalcium phosphate, corn starch